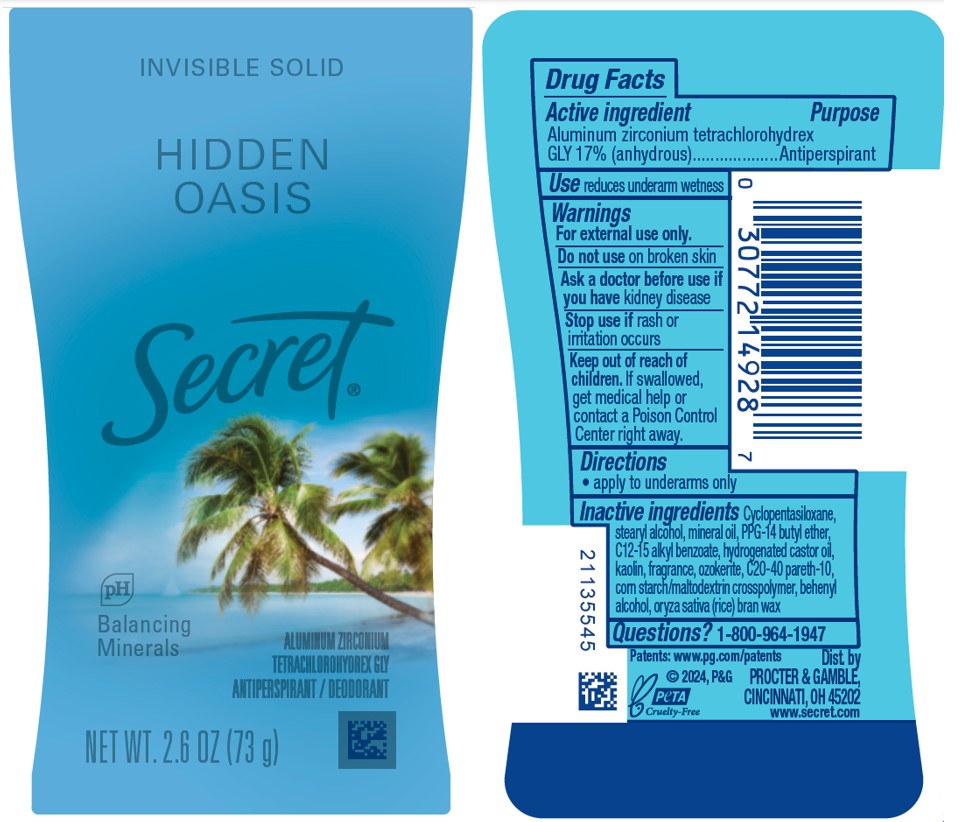 DRUG LABEL: Secret Hidden Oasis Invisible
NDC: 84126-165 | Form: STICK
Manufacturer: The Procter & Gamble Manufacturing Company
Category: otc | Type: HUMAN OTC DRUG LABEL
Date: 20250820

ACTIVE INGREDIENTS: ALUMINUM ZIRCONIUM TETRACHLOROHYDREX GLY 17 g/100 g
INACTIVE INGREDIENTS: KAOLIN; C12-15 ALKYL BENZOATE; MINERAL OIL; PPG-14 BUTYL ETHER; CYCLOPENTASILOXANE; STEARYL ALCOHOL; HYDROGENATED CASTOR OIL; BEHENYL ALCOHOL; CERESIN; C20-40 PARETH-10; ORYZA SATIVA (RICE) BRAN

Secret Hidden Oasis Invisible Solid Antiperspirant/Deodorant

Drug Facts

Active ingredient

Aluminum zirconium tetrachlorohydrex Gly 17% (anhydrous)

Purpose

Antiperspirant

Use

reduces underarm wetness

Warnings

For external use only.

Do not use on broken skin

Ask a doctor before use if you have kidney disease

Stop use if rash or irritation occurs

Keep out of reach of children. If swallowed, get medical help or contact a Poison Control Center right away.

Directions

apply to underarms only

Inactive ingredients

Cyclopentasiloxane, stearyl alcohol, mineral oil, PPG-14 butyl ether, C12-15 alkyl benzoate, hydrogenated castor oil, kaolin, fragrance, ozokerite, C20-40 pareth-10, corn starch/maltodextrin crosspolymer, behenyl alcohol, oryza sativa (rice) bran wax

Questions?

1-800-964-1947

Dist. by Procter & Gamble, Cincinnati, OH 45202.

PRINCIPAL DISPLAY PANEL - 73 g Canister Label

INVISIBLE SOLID

HIDDEN OASIS

Secret®

Aluminum zirconium tetraachlorohydrex GLY
ANTIPERSPIRANT/DEODORANT

Net Wt. 2.6 OZ (73 g)